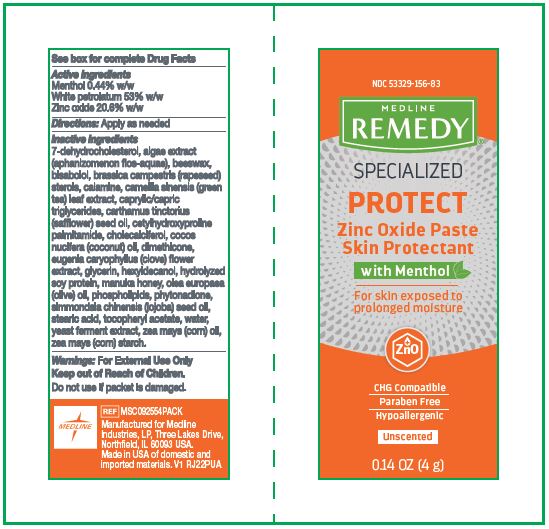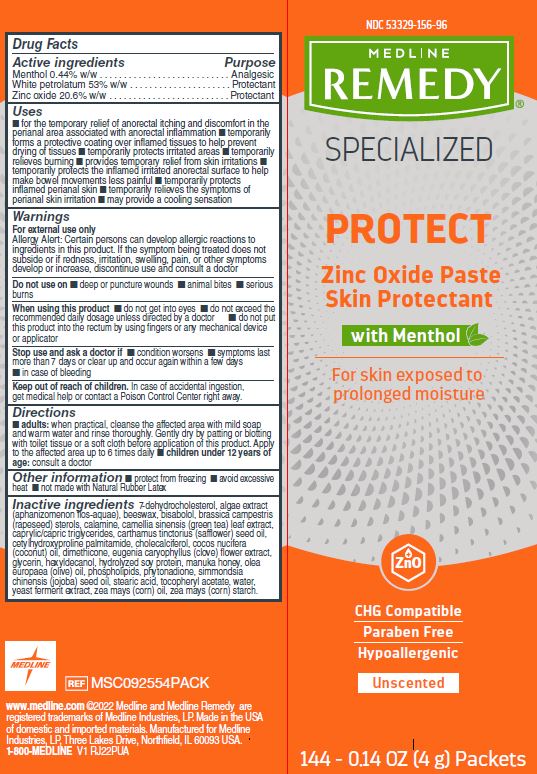 DRUG LABEL: Medline
NDC: 53329-156 | Form: PASTE
Manufacturer: Medline Industries, LP
Category: otc | Type: HUMAN OTC DRUG LABEL
Date: 20251017

ACTIVE INGREDIENTS: ZINC OXIDE 206 mg/1 g; MENTHOL 4.4 mg/1 g; PETROLATUM 530 mg/1 g
INACTIVE INGREDIENTS: MEDIUM-CHAIN TRIGLYCERIDES; HYDROLYZED SOY PROTEIN (ENZYMATIC; 2000 MW); PHYTONADIONE; YEAST, UNSPECIFIED; CORN OIL; ALPHA-TOCOPHEROL ACETATE; CHOLECALCIFEROL; COCONUT OIL; GLYCERIN; HEXYLDECANOL; HONEY; OLIVE OIL; JOJOBA OIL; STEARIC ACID; WATER; GREEN TEA LEAF; CETYLHYDROXYPROLINE PALMITAMIDE; APHANIZOMENON FLOSAQUAE; YELLOW WAX; RAPESEED STEROL; FERRIC OXIDE RED; STARCH, CORN; 7-DEHYDROCHOLESTEROL; LEVOMENOL; SAFFLOWER OIL; DIMETHICONE; CLOVE

156 Remedy Specialized Zinc Oxide Paste

Active ingredients

Menthol 0.44% w/w

White petrolatum 53% w/w

Zinc oxide 20.6% w/w

Purpose

Analgesic

Protectant

Protectant

Uses

- for the temporary relief of anorectal itching and discomfort in the perianal area associated with anorectal inflammation
- temporarily forms a protective coating over inflamed tissues to help prevent drying of tissues
- temporarily protects irritated areas
- temporarily relieves burning
- provides temporary relief from skin irritations
- temporarily protects the inflamed irritated anorectal surface to help make bowel movements less painful
- temporarily protects inflamed perianal skin
- temporarily relieves the symptoms of perianal skin irritation
- may provide a cooling sensation

Warnings

For external use only

Allergy Alert: Certain persons can develop allergic reactions to ingredients in this product. If the symptom being treated does not subside or if redness, irritation, swelling, pain, or other symptoms develop or increase, discontinue use and consult a doctor

Do not use on

- deep or puncture wounds
- animal bites
- serious burns

When using this product

- do not get into eyes
- do not exceed the recommended daily dosage unless directed by a doctor
- do not put this product into the rectum by using fingers or any mechanical device applicator

Stop use and ask a doctor if

- condition worsens
- symptoms last more than 7 days or clear up and occur again within a few days
- in case of bleeding

Keep out of reach of children.

In case of accidental ingestion, get medical help or contact a Poison Control Center right away.

Directions

- adults: when practical, cleanse the affected area with mild soap and warm water and rinse thoroughly. Gently dry by patting or blotting with toilet tissue or a soft cloth before application of this product. Apply to the affected area up to 6 times daily
- Children under 12 years of age: consult a doctor

Other information

- protect from freezing
- avoid excessive heat
- not made with Natural rubber Latex

Inactive ingredients

7-dehydrocholesterol, algae extract (aphanizomenon flos-aquae), beeswax, bisabolol, brassica campestris (rapeseed) sterols, calamine, camellia sinensis (green tea) leaf extract, caprylic/capric triglycerides, carthamus tinctorius (safflower) seed oil, cetylhydroxyproline palmitamide, cholecalciferol, cocos nucifera (coconut) oil, dimethicone, eugenia caryophyllus (clove) flower extract, glycerin, hexyldecanol, hydrolyzed soy protein, manuka honey, olea europaea (olive) oil, phospholipids, phytonadione, simmondsia chinensis (jojoba) seed oil, stearic acid, tocopheryl acetate, water, yeast ferment extract, zea mays (corn) oil, zea mays (corn) starch.

Manufacturing information

Manufactured for:

Medline Industries, LP

Three Lakes Drive, Northfield, IL 60093 USA

Made in USA of domestic and imported materials

1-800-MEDLINE (633-5463)

REF: MSC092554PACK